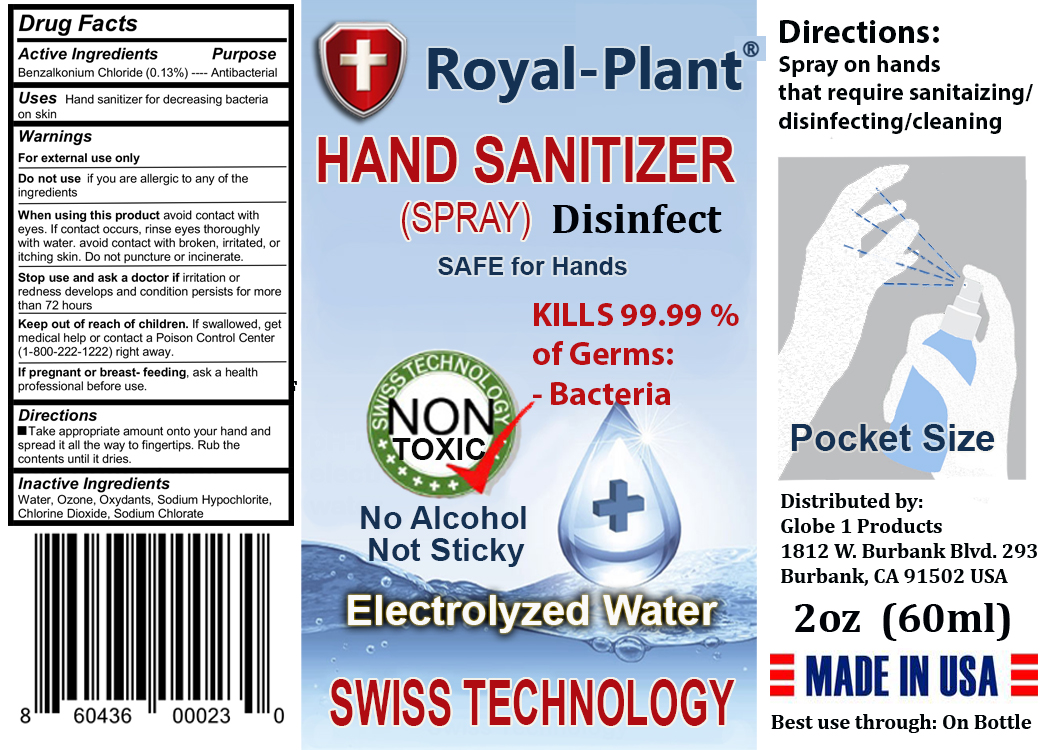 DRUG LABEL: Royal-Plant Hand Sanitizer
NDC: 74606-100 | Form: LIQUID
Manufacturer: Dor Properties LLC.
Category: otc | Type: HUMAN OTC DRUG LABEL
Date: 20200411

ACTIVE INGREDIENTS: BENZALKONIUM CHLORIDE 0.13 g/100 mL
INACTIVE INGREDIENTS: SODIUM CHLORATE; OZONE; CHLORINE DIOXIDE; WATER; SODIUM HYPOCHLORITE

Royal-Plant Hand Sanitizer

Active ingredient

Benzalkonium Chloride (0.13%)

Purpose

Antibacterial

Uses

Hand sanitizer for decreasing bacteria on skin

Warnings

For external use only

Do not use if you are allergic to any of the ingredients

When using this product avoid contact with eyes. If contact occurs, rinse eyes thoroughly with water. avoid contact with broken, irritated, or itching skin. Do not puncture or incinerate.

Stop use and ask a doctor if irritation or redness develops and condition persists for more than 72 hours

If pregnant or breast- feeding, ask a health professional before use.

Keep out of reach of children. If swallowed, get medical help or contact a Poison Control Center (1-800-222-1222) right away.

Directions

Take appropriate amount onto your hand and spread it all the way to fingertips. Rub the contents until it dries.

Inactive ingredient

Water, Ozone, Oxydants, Sodium Hypochlorite, Chlorine Dioxide, Sodium Chlorate